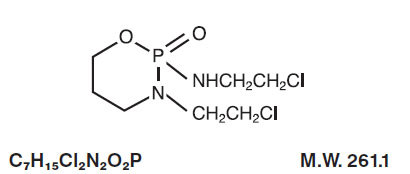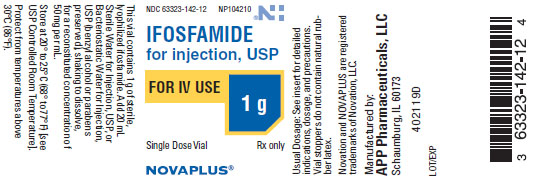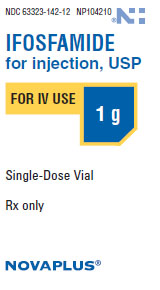 DRUG LABEL: Ifosfamide
NDC: 63323-142 | Form: INJECTION, POWDER, LYOPHILIZED, FOR SOLUTION
Manufacturer: Fresenius Kabi USA, LLC
Category: prescription | Type: HUMAN PRESCRIPTION DRUG LABEL
Date: 20241014

ACTIVE INGREDIENTS: IFOSFAMIDE 1 g/1 1
INACTIVE INGREDIENTS: BENZYL ALCOHOL

Ifosfamide for Injection, USP

Rx only

WARNING

Ifosfamide for Injection, USP should be administered under the supervision of a qualified physician experienced in the use of cancer chemotherapeutic agents. Urotoxic side effects, especially hemorrhagic cystitis, as well as CNS toxicities such as confusion and coma have been associated with the use of ifosfamide. When they occur, they may require cessation of ifosfamide therapy. Severe myelosuppression has been reported (see " ADVERSE REACTIONS").

DESCRIPTION

Ifosfamide for Injection, USP single-dose vials for constitution and administration by intravenous infusion each contain 1 gram or 3 grams of sterile, lyophilized ifosfamide. Ifosfamide is a chemotherapeutic agent chemically related to the nitrogen mustards and a synthetic analog of cyclophosphamide. Ifosfamide is 3-(2-chloroethyl)-2-[(2-chloroethyl)amino] tetrahydro-2H-1,3,2-oxazaphosphorine 2-oxide. Its structural formula is:

Ifosfamide is a white crystalline powder that is soluble in water.

CLINICAL PHARMACOLOGY

Ifosfamide has been shown to require metabolic activation by microsomal liver enzymes to produce biologically active metabolites. Activation occurs by hydroxylation at the ring carbon atom 4 to form the unstable intermediate 4-hydroxyifosfamide. This metabolite rapidly degrades to the stable urinary metabolite 4-ketoifosfamide. Opening of the ring results in formation of the stable urinary metabolite, 4-carboxyifosfamide. These urinary metabolites have not been found to be cytotoxic. N, N- bis (2-chloroethyl)-phosphoric acid diamide (ifosphoramide) and acrolein are also found. Enzymatic oxidation of the chloroethyl side chains, and subsequent dealkylation produces the major urinary metabolites, dechloroethyl ifosfamide and dechloroethyl cyclophosphamide. The alkylated metabolites of ifosfamide have been shown to interact with DNA.

In vitro incubation of DNA with activated ifosfamide has produced phosphotriesters. The treatment of intact cell nuclei may also result in the formation of DNA-DNA cross-links. DNA repair most likely occurs in G-1 and G-2 stage cells.

Pharmacokinetics

Ifosfamide exhibits dose-dependent pharmacokinetics in humans. At single doses of 3.8 to 5 g/m^2, the plasma concentrations decay biphasically and the mean terminal elimination half-life is about 15 hours. At doses of 1.6 to 2.4 g/m^2/day, the plasma decay is monoexponential and the terminal elimination half-life is about 7 hours. Ifosfamide is extensively metabolized in humans and the metabolic pathways appear to be saturated at high doses.

After administration of doses of 5 g/m^2 of^14C-labeled ifosfamide, from 70% to 86% of the dosed radioactivity was recovered in the urine, with about 61% of the dose excreted as parent compound. At doses of 1.6 to 2.4 g/m^2 only 12% to 18% of the dose was excreted in the urine as unchanged drug within 72 hours.

Two different dechloroethylated derivatives of ifosfamide, 4-carboxyifosfamide, thiodiacetic acid and cysteine conjugates of chloroacetic acid have been identified as the major urinary metabolites of ifosfamide in humans and only small amounts of 4-hydroxyifosfamide and acrolein are present. Small quantities (nmole/mL) of ifosfamide mustard and 4-hydroxyifosfamide are detectable in human plasma. Metabolism of ifosfamide is required for the generation of the biologically active species and while metabolism is extensive, it is also quite variable among patients.

In a study at Indiana University, 50 fully evaluable patients with germ cell testicular cancer were treated with Ifosfamide for Injection in combination with cisplatin and either vinblastine or etoposide after failing (47 of 50 patients) at least two prior chemotherapy regimens consisting of cisplatin/vinblastine/bleomycin, (PVB), cisplatin/vinblastine/actinomycin D/bleomycin/ cyclophosphamide, (VAB6), or the combination of cisplatin and etoposide. Patients were selected for remaining cisplatin sensitivity because they had previously responded to a cisplatin containing regimen and had not progressed while on the cisplatin containing regimen or within 3 weeks of stopping it. Patients served as their own control based on the premise that long-term complete responses could not be achieved by retreatment with a regimen to which they had previously responded and subsequently relapsed.

Ten of 50 fully evaluable patients were still alive 2 to 5 years after treatment. Four of the 10 long-term survivors were rendered free of cancer by surgical resection after treatment with the ifosfamide regimen; median survival for the entire group of 50 fully evaluable patients was 53 weeks.

INDICATIONS AND USAGE

Ifosfamide for Injection, used in combination with certain other approved antineoplastic agents, is indicated for third line chemotherapy of germ cell testicular cancer. It should ordinarily be used in combination with a prophylactic agent for hemorrhagic cystitis, such as mesna.

CONTRAINDICATIONS

Continued use of Ifosfamide for Injection is contraindicated in patients with severely depressed bone marrow function (see WARNINGS and PRECAUTIONS sections). Ifosfamide for Injection is also contraindicated in patients who have demonstrated a previous hypersensitivity to it.

WARNINGS

Urinary System

Urotoxic side effects, especially hemorrhagic cystitis, have been frequently associated with the use of ifosfamide. It is recommended that a urinalysis should be obtained prior to each dose of ifosfamide. If microscopic hematuria (greater than 10 RBCs per high power field), is present, then subsequent administration should be withheld until complete resolution.

Further administration of ifosfamide should be given with vigorous oral or parenteral hydration.

Hematopoietic System

When ifosfamide is given in combination with other chemotherapeutic agents, severe myelosuppression is frequently observed. Close hematologic monitoring is recommended. White blood cell (WBC) count, platelet count and hemoglobin should be obtained prior to each administration and at appropriate intervals. Unless clinically essential, ifosfamide should not be given to patients with a WBC count below 2000/μL and/or a platelet count below 50,000/μL.

Central Nervous System

Neurologic manifestations consisting of somnolence, confusion, hallucinations and in some instances, coma, have been reported following ifosfamide therapy. The occurrence of these symptoms requires discontinuing ifosfamide therapy. The symptoms have usually been reversible and supportive therapy should be maintained until their complete resolution.

Pregnancy

Animal studies indicate that the drug is capable of causing gene mutations and chromosomal damage in vivo. Embryotoxic and teratogenic effects have been observed in mice, rats and rabbits at doses 0.05 to 0.075 times the human dose. Ifosfamide can cause fetal damage when administered to a pregnant woman. If ifosfamide is used during pregnancy, or if the patient becomes pregnant while taking this drug, the patient should be apprised of the potential hazard to the fetus.

PRECAUTIONS

General

Ifosfamide should be given cautiously to patients with impaired renal function as well as to those with compromised bone marrow reserve, as indicated by: leukopenia, granulocytopenia, extensive bone marrow metastases, prior radiation therapy, or prior therapy with other cytotoxic agents.

Laboratory Tests

During treatment, the patient’s hematologic profile (particularly neutrophils and platelets) should be monitored regularly to determine the degree of hematopoietic suppression. Urine should also be examined regularly for red cells which may precede hemorrhagic cystitis.

Drug Interactions

The physician should be alert for possible combined drug actions, desirable or undesirable, involving ifosfamide even though ifosfamide has been used successfully concurrently with other drugs, including other cytotoxic drugs.

Wound Healing

Ifosfamide may interfere with normal wound healing.

Pregnancy

Teratogenic Effects: Pregnancy Category D. See WARNINGS.

Nursing Mothers

Ifosfamide is excreted in breast milk. Because of the potential for serious adverse events and the tumorigenicity shown for ifosfamide in animal studies, a decision should be made whether to discontinue nursing or to discontinue the drug, taking into account the importance of the drug to the mother.

Carcinogenesis, Mutagenesis, Impairment of Fertility

Ifosfamide has been shown to be carcinogenic in rats, with female rats showing a significant incidence of leiomyosarcomas and mammary fibroadenomas.

The mutagenic potential of ifosfamide has been documented in bacterial systems in vitro and mammalian cells in vivo. In vivo, ifosfamide has induced mutagenic effects in mice and Drosophila melanogaster germ cells, and has induced a significant increase in dominant lethal mutations in male mice as well as recessive sex-linked lethal mutations in Drosophila.

In pregnant mice, resorptions increased and anomalies were present at day 19 after 30mg/m^2 dose of ifosfamide was administered on day 11 of gestation. Embryolethal effects were observed in rats following the administration of 54 mg/m^2 doses of ifosfamide from the 6th through the 15th day of gestation and embryotoxic effects were apparent after dams received 18 mg/m^2 doses over the same dosing period. Ifosfamide is embryotoxic to rabbits receiving 88 mg/m^2/day doses from the 6th through the 18th day after mating. The number of anomalies was also significantly increased over the control group.

Pediatric Use

Safety and effectiveness in pediatric patients have not been established.

ADVERSE REACTIONS

In patients receiving ifosfamide as a single agent, the dose-limiting toxicities are myelosuppression and urotoxicity. Dose fractionation, vigorous hydration, and a protector such as mesna can significantly reduce the incidence of hematuria, especially gross hematuria, associated with hemorrhagic cystitis. At a dose of 1.2 g/m^2 daily for 5 consecutive days, leukopenia, when it occurs, is usually mild to moderate. Other significant side effects include alopecia, nausea, vomiting, and central nervous system toxicities.

Adverse Reaction | *Incidence; (%)
Alopecia | 83
Nausea-Vomiting | 58
Hematuria | 46
Gross Hematuria | 12
CNS Toxicity | 12
Infection | 8
Renal Impairment | 6
Liver Dysfunction | 3
Phlebitis | 2
Fever | 1
Allergic Reaction | <1
Anorexia | <1
Cardiotoxicity | <1
Coagulopathy | <1
Constipation | <1
Dermatitis | <1
Diarrhea | <1
Fatigue | <1
Hypertension | <1
Hypotension | <1
Malaise | <1
Polyneuropathy | <1
Pulmonary Symptoms | <1
Salivation | <1
Stomatitis | <1

*Based upon 2,070 patients from the published literature in 30 single agent studies.

Hematologic Toxicity

Myelosuppression was dose related and dose limiting. It consisted mainly of leukopenia and, to a lesser extent, thrombocytopenia. A WBC count <3000/μL is expected in 50% of the patients treated with ifosfamide single agent at doses of 1.2 g/m^2 per day for 5 consecutive days. At this dose level, thrombocytopenia (platelets <100,000/μL) occurred in about 20% of the patients. At higher dosages, leukopenia was almost universal, and at total dosages of 10 to 12 g/m^2/cycle, one half of the patients had a WBC count below 1000/μL and 8% of patients had platelet counts less than 50,000/μL. Myelosuppression was usually reversible and treatment can be given every 3 to 4 weeks. When ifosfamide is used in combination with other myelosuppressive agents, adjustments in dosing may be necessary. Patients who experience severe myelosuppression are potentially at increased risk for infection. Anemia has been reported as part of postmarketing surveillance.

Digestive System

Nausea and vomiting occurred in 58% of the patients who received ifosfamide. They were usually controlled by standard antiemetic therapy. Other gastrointestinal side effects include anorexia, diarrhea, and in some cases, constipation.

Urinary System

Urotoxicity consisted of hemorrhagic cystitis, dysuria, urinary frequency and other symptoms of bladder irritation. Hematuria occurred in 6% to 92% of patients treated with ifosfamide. The incidence and severity of hematuria can be significantly reduced by using vigorous hydration, a fractionated dose schedule and a protector such as mesna. At daily doses of 1.2 g/m^2 for 5 consecutive days without a protector, microscopic hematuria is expected in about one half of the patients and gross hematuria in about 8% of patients.

Renal toxicity occurred in 6% of the patients treated with ifosfamide as a single agent. Clinical signs, such as elevation in BUN or serum creatinine or decrease in creatinine clearance, were usually transient. They were most likely to be related to tubular damage. One episode of renal tubular acidosis which progressed into chronic renal failure was reported. Proteinuria and acidosis also occurred in rare instances. Metabolic acidosis was reported in 31% of patients in one study when ifosfamide was administered at doses of 2 to 2.5 g/m^2/day for 4 days. Renal tubular acidosis, Fanconi syndrome, renal rickets, and acute renal failure have been reported. Close clinical monitoring of serum and urine chemistries including phosphorus, potassium, alkaline phosphatase and other appropriate laboratory studies is recommended. Appropriate replacement therapy should be administered as indicated.

Central Nervous System

CNS side effects were observed in 12% of patients treated with ifosfamide. Those most commonly seen were somnolence, confusion, depressive psychosis, and hallucinations. Other less frequent symptoms include dizziness, disorientation, and cranial nerve dysfunction. Seizures and coma with death were occasionally reported. The incidence of CNS toxicity may be higher in patients with altered renal function.

Other

Alopecia occurred in approximately 83% of the patients treated with ifosfamide as a single agent. In combination, this incidence may be as high as 100%, depending on the other agents included in the chemotherapy regimen. Increases in liver enzymes and/or bilirubin were noted in 3% of the patients. Other less frequent side effects included phlebitis, pulmonary symptoms, fever of unknown origin, allergic reactions, stomatitis, cardiotoxicity, and polyneuropathy.

OVERDOSAGE

No specific antidote for ifosfamide is known. Management of overdosage would include general supportive measures to sustain the patient through any period of toxicity that might occur.

DOSAGE AND ADMINISTRATION

Ifosfamide for Injection should be administered intravenously at a dose of 1.2 g/m^2 per day for 5 consecutive days. Treatment is repeated every 3 weeks or after recovery from hematologic toxicity (Platelets ≥100,000/μL, WBC ≥4,000/μL). In order to prevent bladder toxicity, Ifosfamide for Injection should be given with extensive hydration consisting of at least 2 liters of oral or intravenous fluid per day. A protector, such as mesna, should also be used to prevent hemorrhagic cystitis. Ifosfamide for Injection should be administered as a slow intravenous infusion lasting a minimum of 30 minutes. Although Ifosfamide for Injection has been administered to a small number of patients with compromised hepatic and/or renal function, studies to establish optimal dose schedules of Ifosfamide for Injection in such patients have not been conducted.

Preparation for Intravenous Administration/Stability

Injections are prepared for parenteral use by adding Sterile Water for Injection, USP, or Bacteriostatic Water for Injection, USP (benzyl alcohol or parabens preserved), to the vial and shaking to dissolve. Use the quantity of diluent shown below to constitute the product:

Dosage; Strength | Quantity of; Diluent | Final; Concentration
1 gram | 20 mL | 50 mg/mL
3 grams | 60 mL | 50 mg/mL

Solutions of ifosfamide may be diluted further to achieve concentrations of 0.6 to 20 mg/mL in the following fluids:

5% Dextrose Injection, USP

0.9% Sodium Chloride Injection, USP

Lactated Ringer’s Injection, USP

Sterile Water for Injection, USP

Because essentially identical stability results were obtained for Sterile Water admixtures as for the other admixtures (5% Dextrose Injection, 0.9% Sodium Chloride Injection, and Lactated Ringer’s Injection), the use of large volume parenteral glass bottles, Viaflex bags or PAB™ bags that contain intermediate concentrations or mixtures of excipients (e.g., 2.5% Dextrose Injection, 0.45% Sodium Chloride Injection, or 5% Dextrose and 0.9% Sodium Chloride Injection) is also acceptable.

Constituted or constituted and further diluted solutions of Ifosfamide for Injection should be refrigerated and used within 24 hours.

Parenteral drug products should be inspected visually for particulate matter and discoloration prior to administration.

HOW SUPPLIED

Ifosfamide for Injection, USP, lyophilized is available as:

Product; No. | NDC; No.
NP104210 | 63323-142-12 | Ifosfamide for Injection, USP, 1 gram single-dose vial, packaged individually.
NP104300 | 63323-143-12 | Ifosfamide for Injection, USP, 3 gram single-dose vial, packaged individually.

Store at 20° to 25°C (68° to 77°F) [see USP Controlled Room Temperature].

Vial stoppers do not contain natural rubber latex.

Protect from temperatures above 30°C (86°F).

Procedures for proper handling and disposal of anticancer drugs should be considered. Skin reactions associated with accidental exposure to Ifosfamide for Injection may occur. The use of gloves is recommended. If Ifosfamide for Injection solution contacts the skin or mucosa, immediately wash the skin thoroughly with soap and water or rinse the mucosa with copious amounts of water. Several guidelines on this subject have been published.^1-7 There is no general agreement that all of the procedures recommended in the guidelines are necessary or appropriate.

REFERENCES

1. Recommendations for the Safe Handling of Parenteral Antineoplastic Drugs. NIH Publication No. 83-2621. For sale by the Superintendent of Documents, U.S. Government Printing Office, Washington, DC 20402.
2. AMA Council Report. Guidelines for Handling Parenteral Antineoplastics. JAMA 1985; 253 (11):1590-1592.
3. National Study Commission on Cytotoxic Exposure-Recommendations for Handling Cytotoxic Agents. Available from Louis P. Jeffrey, Sc. D., Chairman, National Study Commission on Cytotoxic Exposure, Massachusetts College of Pharmacy and Allied Health Sciences, 179 Longwood Avenue, Boston, Massachusetts 02115.
4. Clinical Oncological Society of Australia: Guidelines and Recommendations for Safe Handling of Antineoplastic Agents. Med J Australia 1983; 1:426-428.
5. Jones, RB, et al: Safe Handling of Chemotherapeutic Agents: A Report from the Mount Sinai Medical Center, CA-A Cancer Journal for Clinicians 1983; (Sept./Oct.) 258-263.
6. American Society of Hospital Pharmacists Technical Assistance Bulletin on Handling Cytotoxic and Hazardous Drugs. Am J Hosp Pharm 1990;47:1033-1049.
7. Controlling Occupational Exposure to Hazardous Drugs. (OSHA WORK-PRACTICE GUIDELINES). Am J Health-Syst Pharm 1996; 53:1669-1685.

Manufactured by:

APP Pharmaceticals, LLC

Schaumburg, IL 60173

45977B

Revised: April 2008

PACKAGE LABEL

PACKAGE LABEL - PRINCIPAL DISPLAY - Ifosfamide 1 g Single Dose Vial Label

NDC 63323-142-12

NP104210

Ifosfamide for Injection, USP

1 g

For IV Use

Single-Dose Vial

Rx only

PACKAGE LABEL - PRINCIPAL DISPLAY - Ifosfamide 1 g Single Dose Vial Carton Panel

NDC 63323-142-12

NP104210

Ifosfamide for Injection, USP

1 g

For IV Use

Single-Dose Vial

Rx only